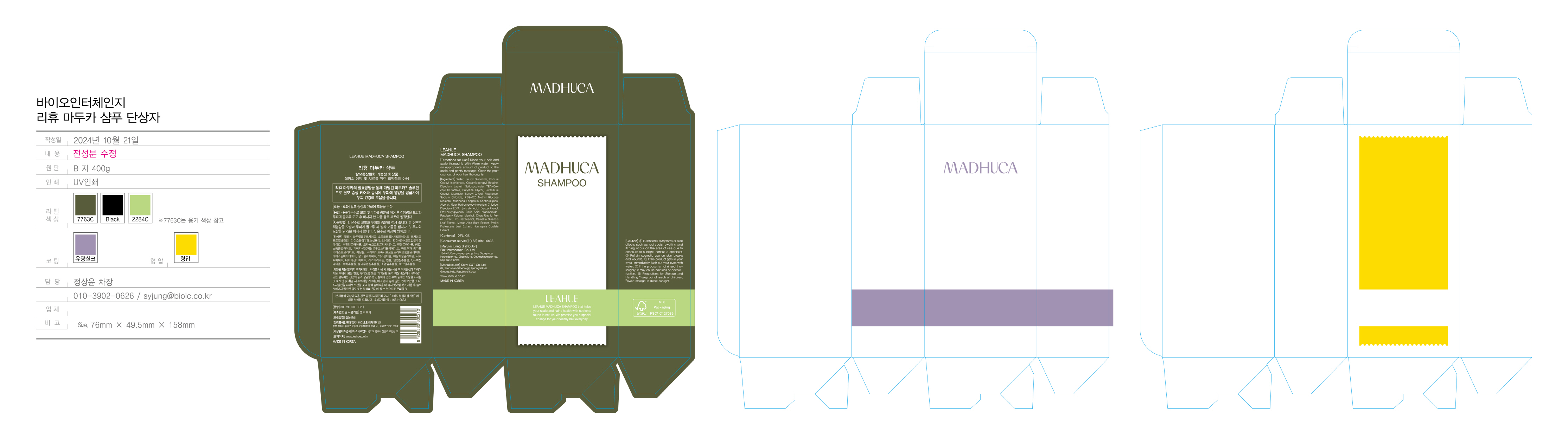 DRUG LABEL: LEAHUE MADHUCA
NDC: 72837-0002 | Form: SHAMPOO
Manufacturer: Bio-interchange Co.
Category: otc | Type: HUMAN OTC DRUG LABEL
Date: 20250404

ACTIVE INGREDIENTS: SALICYLIC ACID 0.2 g/100 mL
INACTIVE INGREDIENTS: MENTHOL; ALCOHOL

Active Ingredient

Salicylic Acid

Inactive Ingredients

Menthol, Water, Alcohol, etc

Purpose

Leahue Shampoo removes sebum and impurities from the scalp. to relieve the symptoms of hair loss

Keep out of reach of children

Indications & Usage

Rinse your hair and scalp thoroughly with warm water. Apply an appropriate amount of product to the scalp and gently massage. Clean the product out of your hair thoroughly.

Warnings (Cautions)

1. If abnormal symptoms or side effects such as red spots, swelling and itching occur on the area of use due to exposure to sunlight, consult a specialist.
2. Refrain cosmetic use on skin breaks and wounds.
3. If the product gets in your eyes, immediately flush out your eyes with water.
4. If the product is not rinsed thoroughly, it may cause hair loss or decolorization.
5. Storage and Precautions for Handling *Keep out of reach of children. *Avoid storage in direct sunlight.

DOSAGE AND ADMINISTRATION

For external use only